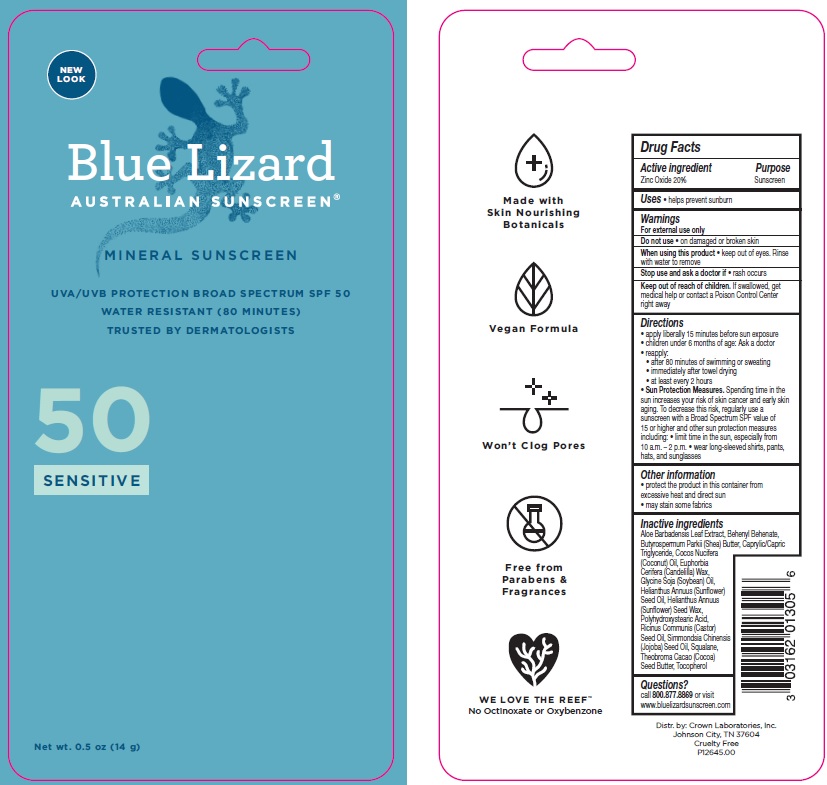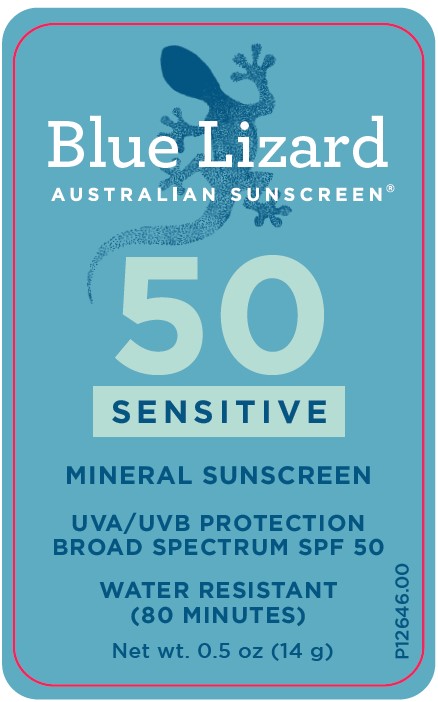 DRUG LABEL: Blue Lizard Sensitive SPF 50
NDC: 0316-2013 | Form: STICK
Manufacturer: Crown Laboratories
Category: otc | Type: HUMAN OTC DRUG LABEL
Date: 20260112

ACTIVE INGREDIENTS: ZINC OXIDE 20 mg/1 g
INACTIVE INGREDIENTS: SOYBEAN OIL; BEHENYL BEHENATE; COCONUT OIL; POLYHYDROXYSTEARIC ACID STEARATE; CASTOR OIL; .ALPHA.-TOCOPHEROL, D-; JOJOBA OIL; ALOE VERA LEAF; MEDIUM-CHAIN TRIGLYCERIDES; SUNFLOWER OIL; COCOA BUTTER; HELIANTHUS ANNUUS SEED WAX; CANDELILLA WAX; SQUALANE; SHEA BUTTER

Blue Lizard Sensitive SPF 50 Sunscreen Stick

Active ingredient

Zinc Oxide 20%

Purpose

Sunscreen

Uses

- helps prevent sunburn

Warnings

For external use only

Do not use

- on damaged or broken skin

When using this product

- keep out of eyes. Rinse with water to remove

Stop use and ask a doctor if

- rash occurs

Keep out of reach of children

- if swallowed, get medical help or contact a Poison Control Center right away

Directions

• apply liberally 15 minutes before sun exposure

• children under 6 months of age: Ask a doctor

• reapply:

- after 80 minutes of swimming or sweating
- immediately after towel drying
- at least every 2 hours

• Sun Protection Measures. Spending time in the sun increases your risk of skin cancer and early skin aging. To decrease this risk, regularly use a sunscreen with a Broad Spectrum SPF value of 15 or higher and other sun protection measures including:

- limit time in the sun especially from 10 a.m.- 2 p.m.
- wear long-sleeved shirts, pants, hats, and sunglasses

Other information

- protect the product in this container from excessive heat and direct sun
- may stain some fabrics

Inactive ingredients

Aloe Barbadensis Leaf Extract, Behenyl Behenate, Butyrospermum Parkii (Shea) Butter, Caprylic/Capric Triglyceride, Cocos Nucifera (Coconut) Oil, Euphorbia Cerifera (Candelilla) Wax, Glycine Soja (Soybean) Oil, Helianthus Annuus (Sunflower) Seed Oil, Helianthus Annuus (Sunflower) Seed Wax, Polyhydroxystearic Acid, Ricinus Communis (Castor) Seed Oil, Simmondsia Chinensis (Jojoba) Seed Oil, Squalane, Theobroma Cacao (Cocoa) Seed Butter, Tocopherol

Questions?

Call 800.877.8869 or visit www.bluelizardsunscreen.com

Blue Lizard Sensitive SPF 50 Stick Label

BLUE LIZARD

AUSTRALIAN SUNSCREEN

50

SENSITIVE

MINERAL SUNSCREEN

UVA/UVB PROTECTION

BROAD SPECTRUM SPF 50

WATER RESISTANT (80 Minutes)

Net wt. 0.5 oz (14 g)